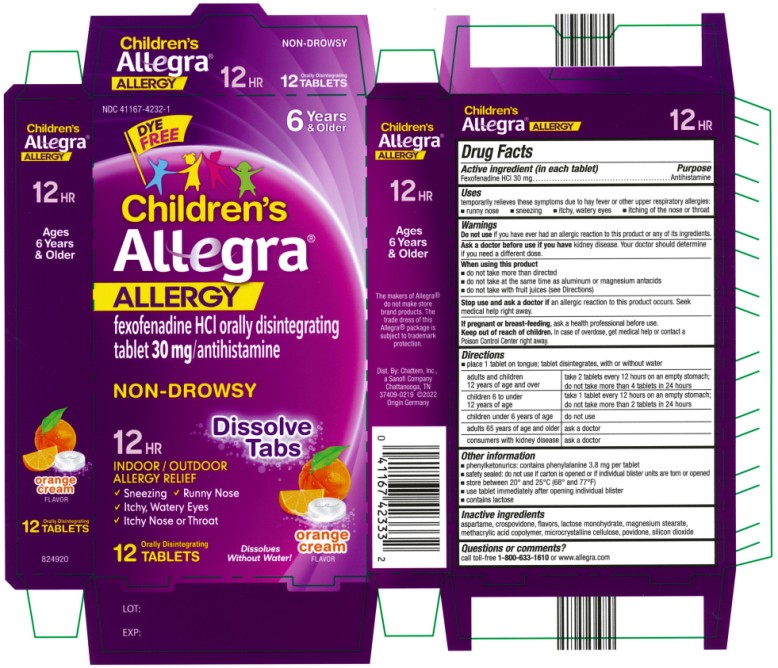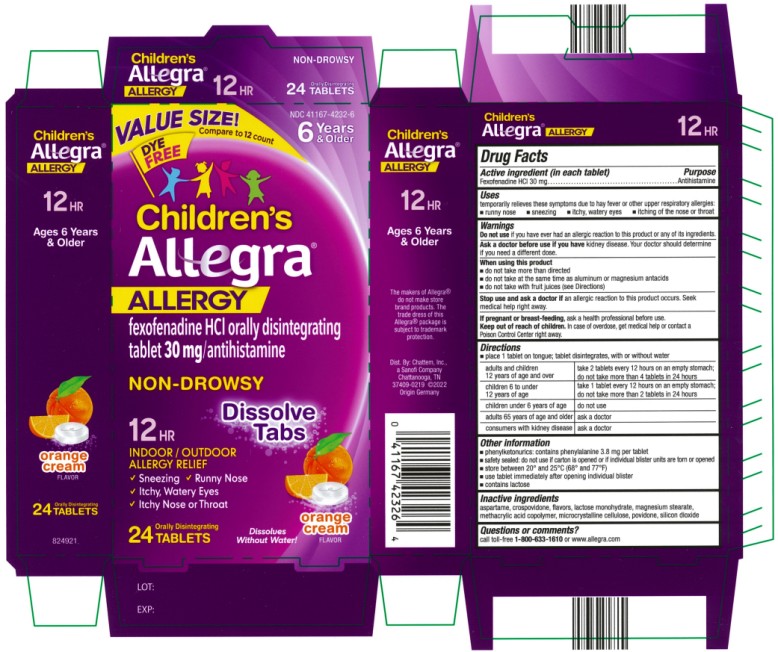 DRUG LABEL: Childrens Allegra Allergy
NDC: 41167-4232 | Form: TABLET, ORALLY DISINTEGRATING
Manufacturer: Chattem, Inc.
Category: otc | Type: HUMAN OTC DRUG LABEL
Date: 20250218

ACTIVE INGREDIENTS: FEXOFENADINE HYDROCHLORIDE 30 mg/1 1
INACTIVE INGREDIENTS: ASPARTAME; CROSPOVIDONE; LACTOSE MONOHYDRATE; MAGNESIUM STEARATE; METHACRYLIC ACID AND ETHYL ACRYLATE COPOLYMER; CELLULOSE, MICROCRYSTALLINE; POVIDONE; SILICON DIOXIDE

Childrens Allegra Allergy

Drug Facts

Active ingredient

(in each tablet)

Fexofenadine HCI 30 mg

Purpose

Antihistamine

Uses

temporarily relieves these symptoms due to hay fever or other upper respiratory allergies:

- runny nose
- sneezing
- itchy, water eyes
- itching of the nose or throat

Warnings

Do not use

if you have ever had an allergic reaction to this product or any of its ingredients.

Ask a doctor before use if you have

kidney disease. Your doctor should determine if you need a different dose.

When using this product

- do not take more than directed
- do not take at the same time as aluminum or magnesium antacids
- do not take with fruit juices (see Directions)

Stop use and ask a doctor if

an allergic reaction to this product occurs. Seek medical help right away.

If pregnant or breast-feeding,

ask a health professional before use.

Keep out of reach of children.

In case of overdose, get medical help or contact a Poison Control Center right away.

Directions

- place 1 tablet on tongue; tablet disintegrates, with or without water

adults and children 12 years of age and over | take 2 tablets every 12 hours on an empty stomach; do not take more than 4 tablets in 24 hours
children 6 to under 12 years of age | take 1 tablet every 12 hours on an empty stomach; do not take more than 2 tablets in 24 hours
children under 6 years of age | do not use
adults 65 years of age and older | ask a doctor
consumers with kidney disease | ask a doctor

Other information

- phenylketonurics: contains phenylalanine 3.8 mg per tablet
- safety sealed: do not use if carton is opened or if individual blister units are torn or opened
- store between 20º and 25ºC (68º and 77ºF)
- use tablet immediately after opening individual blister
- contains lactose

Inactive ingredients

aspartame, crospovidone, flavors, lactose monohydrate, magnesium stearate, methacrylic acid copolymer, microcrystalline cellulose, povidone, silicon dioxide

Questions or comments?

call toll-free 1-800-633-1610 or www.allegra.com

Dist. By: Chattem, Inc, a Sanofi Company,

Chattanooga, TN 37409-0219 ©2015

PRINCIPAL DISPLAY PANEL

NDC 41167-4232-1
NON-DROWSY
Children’s
Allegra®
Allergy
fexofenadine HCl orally disintegrating
tablet 30 mg/antihistamine
Indoor and Outdoor Allergies
Orange Cream flavor
12 Orally Disintegrating Tablets

PRINCIPAL DISPLAY PANEL

NDC 41167-4232-6
NON-DROWSY
Children’s
Allegra®
Allergy
fexofenadine HCl orally disintegrating
tablet 30 mg/antihistamine
Indoor and Outdoor Allergies
Orange Cream flavor
24 Orally Disintegrating Tablets